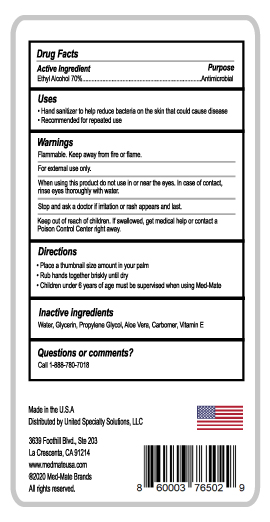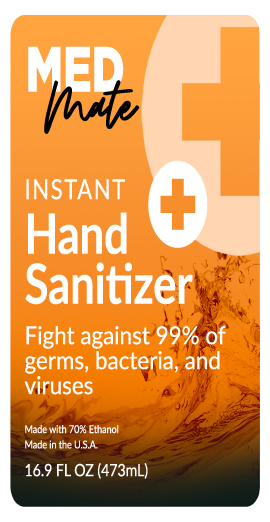 DRUG LABEL: MED Mate Instant Hand Sanitizer
NDC: 80263-001 | Form: GEL
Manufacturer: United Specialty Solutions
Category: otc | Type: HUMAN OTC DRUG LABEL
Date: 20200825

ACTIVE INGREDIENTS: ALCOHOL 70 mL/100 mL
INACTIVE INGREDIENTS: .ALPHA.-TOCOPHEROL; GLYCERIN; WATER; PROPYLENE GLYCOL; ALOE VERA LEAF; CARBOMER HOMOPOLYMER, UNSPECIFIED TYPE

MED Mate Instant Hand Sanitizer

Active Ingredient(s)

Ethyl Alcohol 70%. Purpose: Antimicrobial

Purpose

Antimicrobial, Hand Sanitizer

Use

Hand Sanitizer to help reduce bacteria on the skin that could cause disease

Recommended for repeated use,

Warnings

Flammable. Keep away from heat or flame.

For external use only.

When using this product do not use in or near the eyes. In case of contact, rinse eyes throughly with water.

Stop and ask a doctor if irritation or rash appears and last.

Keep out of reach of children. If swallowed, get medical help or contact a Poison Control Center right away.

Directions

- Place a thumbnail size amount in your palm.
- Rub hands together briskly until dry.
- Children under 6 years of age must be supervised when using Med-Made

Inactive ingredients

Water, Glycerin, Propylene Glycol, Aloe Vera, Carbomer, Vitamin E

Questions or comments?

Call 1-888-760-7018

Package Label - Principal Display Panel

MED MAte

Instant Hand Sanitizer

Fight against 99% of germs, bacteria, and viruses

Made with 70% Ethanol

Made in the U.S.A.

16.9 FL OZ (473mL)